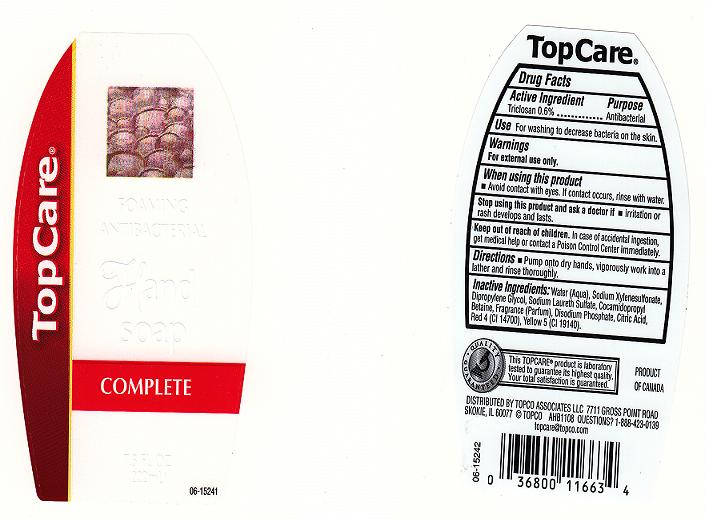 DRUG LABEL: TopCare
NDC: 36800-168 | Form: SOAP
Manufacturer: Topco Associates llc
Category: otc | Type: HUMAN OTC DRUG LABEL
Date: 20100722

ACTIVE INGREDIENTS: TRICLOSAN 0.6 mL/100.0000 mL

Drug Facts Box - Back Label

Active Ingredient

Triclosan 0.6%

Purpose

Antibacterial

Warnings

For external use only

When using this product

- avoid contact with eyes. If contact occurs, rinse eyes with water

Stop using this product and ask doctor if

- irritation or redness develops and lasts

Keep out of reach of children

-in case of accidental ingestion, get medical help or contact a Poison Control Center immediately

Uses

For washing to decrease bacteria on the skin

Directions

Apply onto dry hands, work into rich foamy lather, rinse and dry thoroughly

Inactive Ingredients

Water (Aqua), Sodium Xylenesulfonate, Dipropylene Glycol, Ammonium Lauryl Sulfate, Cocamidopropyl Betaine, Fragrance(Parfum), Disodium Phosphate, Citric Acid, Yellow 5 (CI 19140), Red 40 (CI 16035).

Package Front and Back Labels

7.5 OZ Front and Back Labels: tcare8.jpg